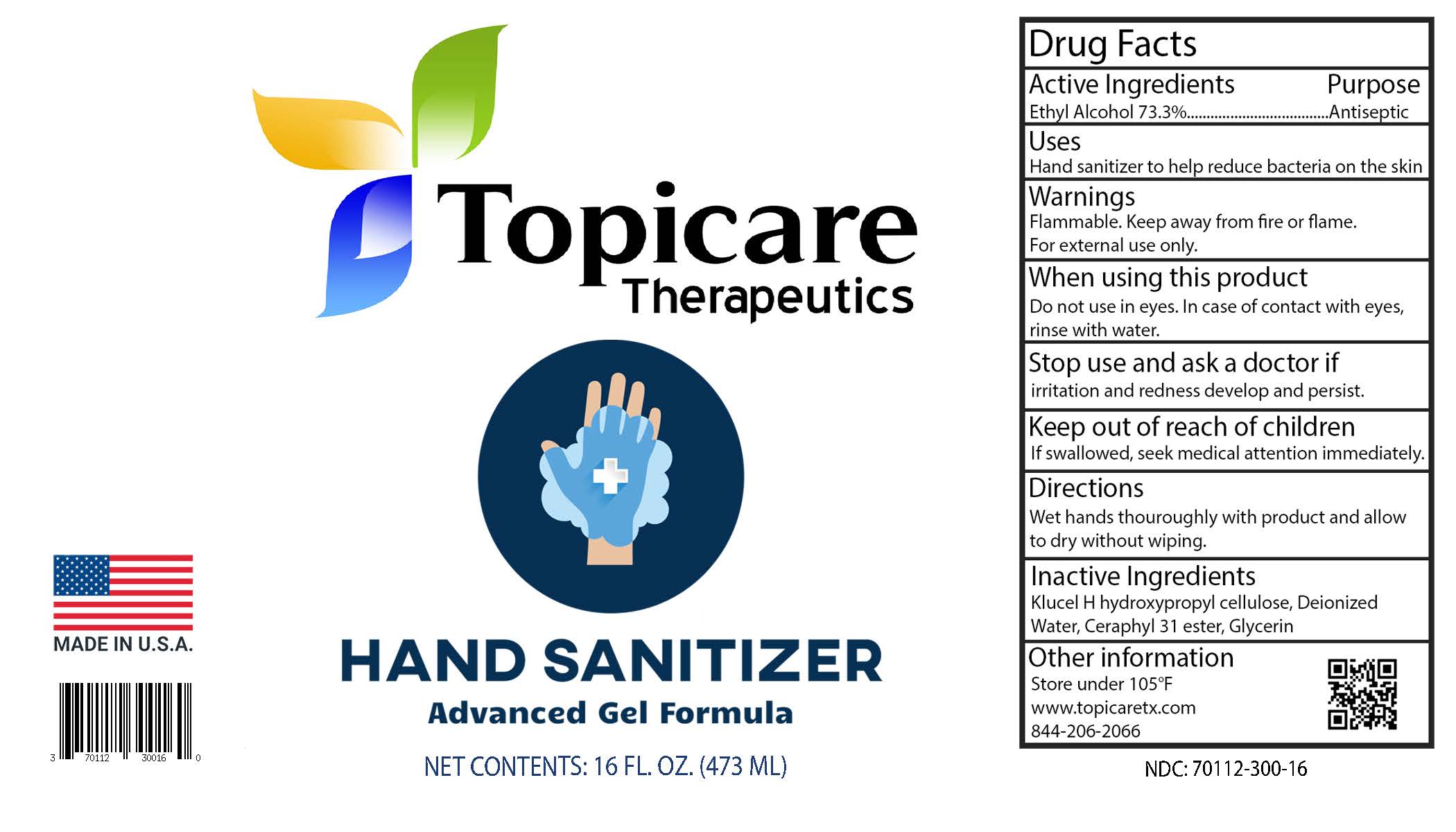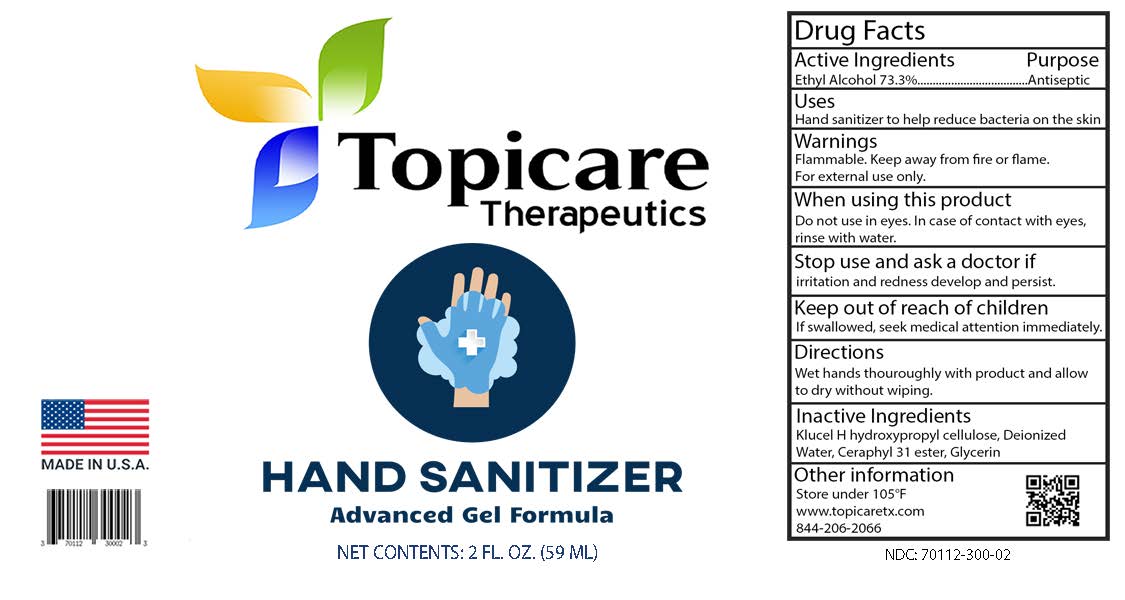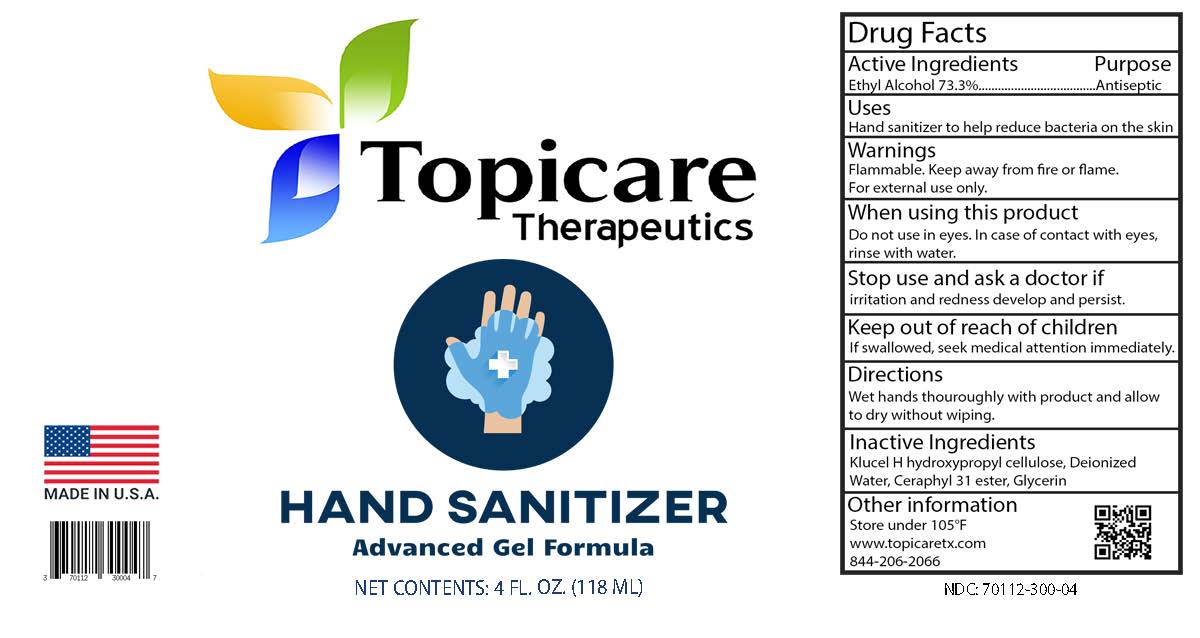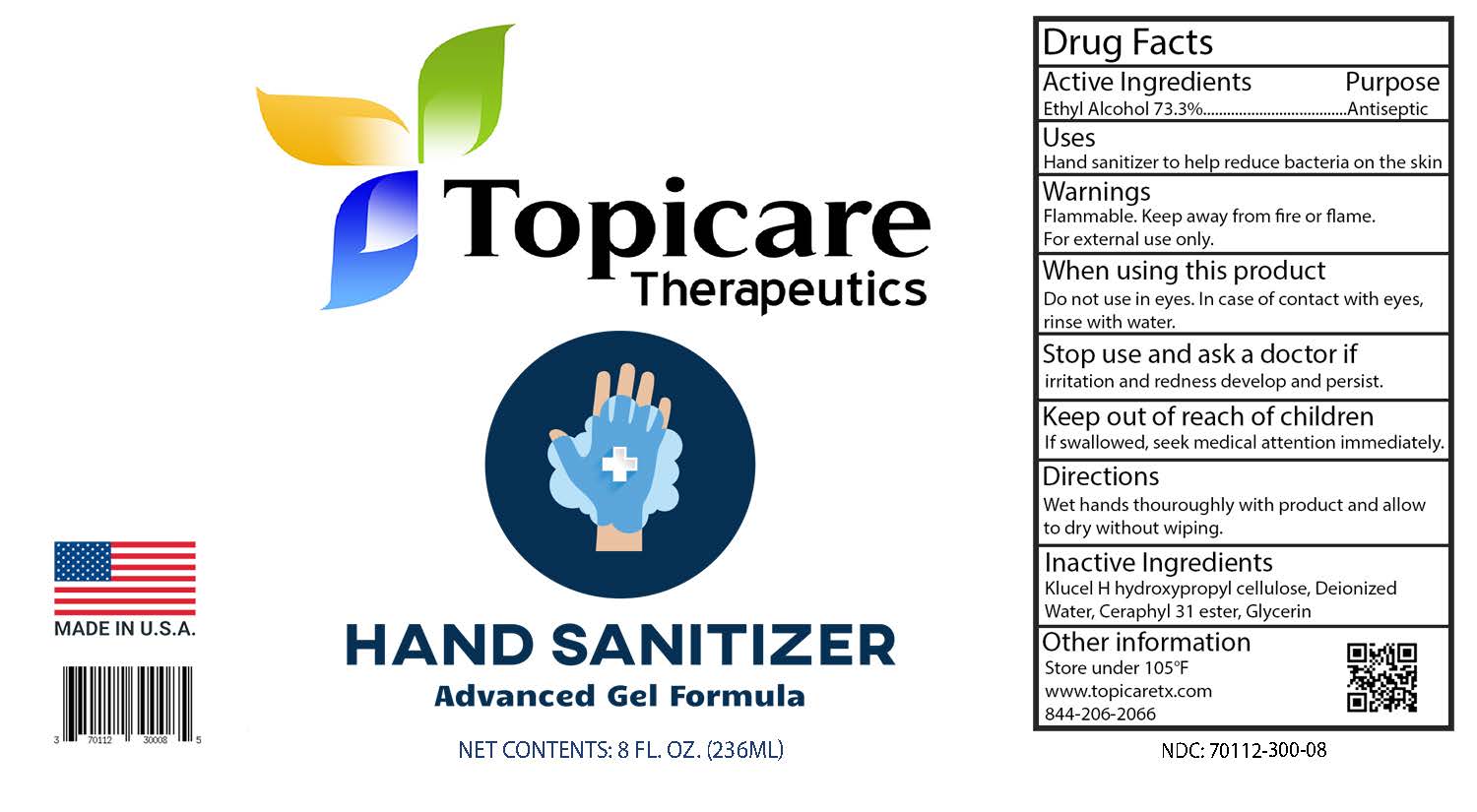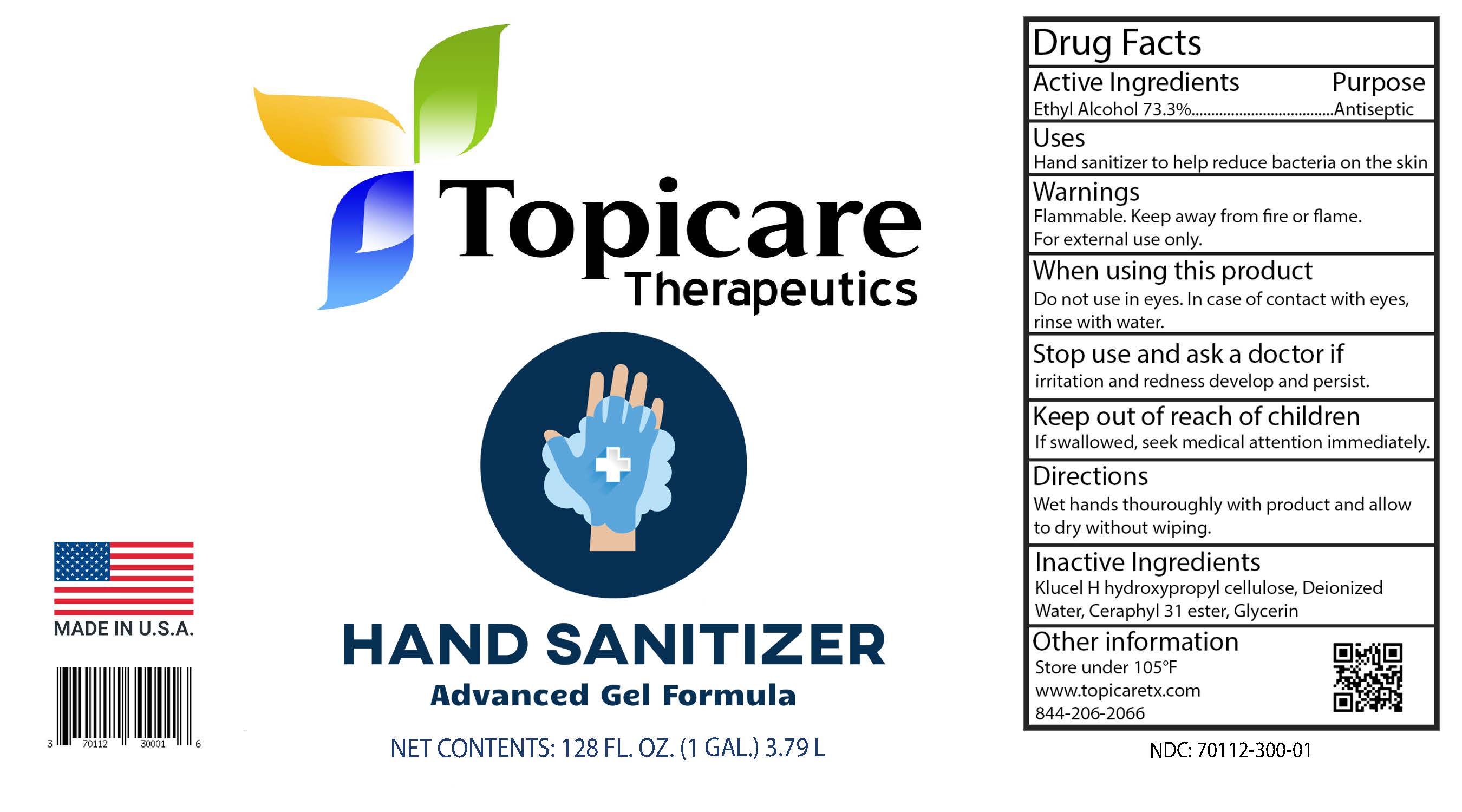 DRUG LABEL: Topicare Therapeutics Hand Sanitizer
NDC: 70112-300 | Form: GEL
Manufacturer: Topicare Management, LLC
Category: otc | Type: HUMAN OTC DRUG LABEL
Date: 20200916

ACTIVE INGREDIENTS: ALCOHOL 73.3 mL/100 mL
INACTIVE INGREDIENTS: GLYCERIN; WATER; MYRISTYL LACTATE; LAURYL LACTATE; HYDROXYPROPYL CELLULOSE, UNSPECIFIED; CETYL LACTATE

Topicare Therapeutics Hand Sanitizer

Active Ingredient(s)

Ethyl Alcohol 73.3%

Purpose

Antiseptic, Hand Sanitizer

Use

Hand Sanitizer to help reduce bacteria that potentially can cause disease.

Warnings

For external use only. Flammable. Keep away from heat or flame

Do not use

On children less than 2 months of age.

On open skin wounds.

When using this product keep out of eyes, ears, and mouth. In case of contact with eyes, rinse eyes thoroughly with water.
Stop use and ask a doctor if irritation or rash occurs.
Keep out of reach of children. If swallowed, get medical help or contact a Poison Control Center right away.

Stop use and ask a doctor if irritation or rash occurs.

Keep out of reach of children. If swallowed, get medical help or contact a Poison Control Center right away.

Directions

Wet hands thoroughly with product and allow to dry without wiping.

Other information

Store between 15-30°C (59-86°F)

Avoid freezing and excessive heat above 40°C (104°F)

Inactive ingredients

Klucel H hydroxypropyl cellulose, Deionized Water, Ceraphyl 31 ester, Glycerin

Package Label - Principal Display Panel

59mL NDC: 70112-300-02

118mL NDC 70112-300-04

236mL NDC 70112-300-08

473mL NDC 70112-300-16

3.79L NDC 70112-300-01